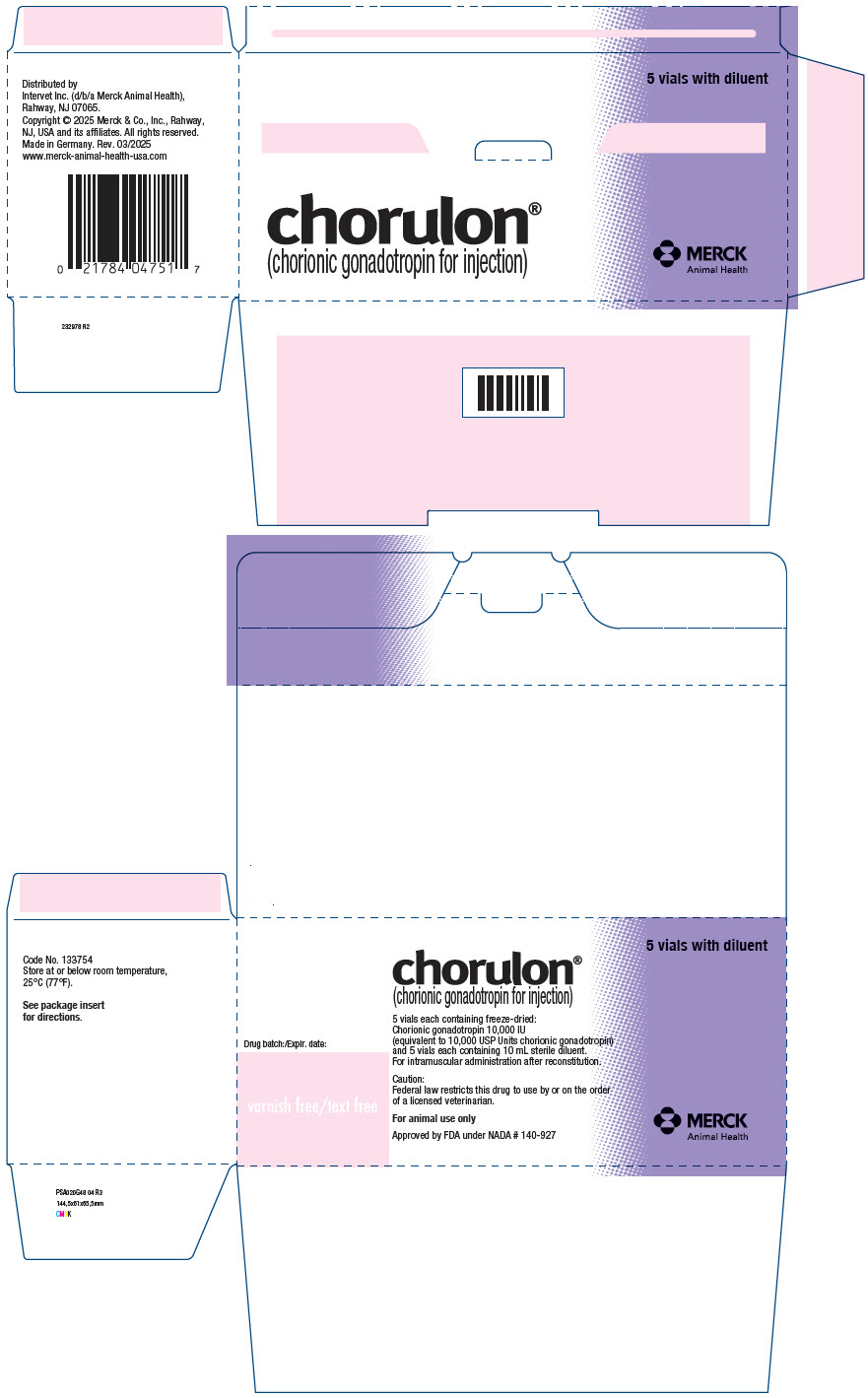 DRUG LABEL: CHORULON
NDC: 57926-475 | Form: KIT | Route: INTRAMUSCULAR
Manufacturer: Merck Sharp & Dohme Corp.
Category: animal | Type: PRESCRIPTION ANIMAL DRUG LABEL
Date: 20260219

ACTIVE INGREDIENTS: CHORIONIC GONADOTROPIN 10000 [iU]/1 1
INACTIVE INGREDIENTS: WATER

CHORULON®

(chorionic gonadotropin for injection)

Approved by FDA under NADA # 140-927

FOR ANIMAL USE ONLY

PRECAUTIONS

CAUTION

Federal law restricts this drug to use by or on the order of a licensed veterinarian.

DESCRIPTION

CHORULON® is a freeze-dried preparation of chorionic gonadotropin (human Chorionic Gonadotropin or hCG) for intramuscular administration after reconstitution. When reconstituted with the accompanying sterile diluent, each 10 mL vial contains 10,000 IU chorionic gonadotropin (equivalent to 10,000 USP Units chorionic gonadotropin) and 10 mg mannitol, with mono- and disodium phosphate to adjust the pH of the solution.

ACTION

Chorionic gonadotropin has luteinizing hormone-like activity with little or no follicle stimulating or estrogenic activity. Product does not conform to the USP monograph for estrogenic activity. Demonstration of the lack of estrogenic activity is performed at the drug substance level.

INDICATIONS

COWS: CHORULON® is indicated for intramuscular use in cows for the treatment of nymphomania (frequent or constant heat) due to cystic ovaries.

FINFISH: CHORULON® is indicated for use as an aid in improving spawning function in male and female brood finfish.

DOSAGE AND ADMINISTRATION

To reconstitute, transfer the contents of one vial of sterile diluent into one vial of freeze-dried powder. The resulting 10 mL of CHORULON® contains 10,000 IU chorionic gonadotropin.

COWS: The contents of one vial (10 mL) of reconstituted CHORULON® should be administered as a single deep intramuscular injection. Dosage may be repeated in 14 days if the animal's behavior or rectal examination of the ovaries indicates the necessity for retreatment.

FINFISH: CHORULON® should be administered via intramuscular injection just ventral to the dorsal fin for one (1) to three (3) injections. Any single injection should be administered, depending on the fish species, at a dose of 50 to 510 IU/lb body weight (bw) for males and 67 to 1816 IU/lb bw for females. Depending on body weight and dose administered, it may be necessary to divide the dose among two or more injection sites to avoid injecting a large volume at a single site.

Summaries of doses tested in representative fish species are contained within the following tables. The dose of CHORULON® to be used in other species of finfish may differ from those species listed in the tables, but should fall within the suggested range of 50 to 510 IU/lb bw for males and 67 to 1816 IU/lb bw for females.

Table 1: Tested Fish Species/Dose Combinations Found to be Effective
Nomenclature Common Name, Genus & Species, Family | Tested Dose(s) (IU/lb bw/injection) |  | Number of Injections | Injections Interval (h)
Nomenclature Common Name, Genus & Species, Family | Males | Females
yellow perch, Perca flavescens, Percidae | nt^1 | 67-300 | 1 | -
striped bass, Morone saxitilis, Percichthyidae | 50-500 | 75-252 | 1 | -
white bass, Morone chrysops, Percichthyidae | 65-510 | 91-750 | 1 | -
razorback sucker, Xyrauchen texanus, Catostomidae | nt [nt = not tested] | 100 | 3 | 24
walleye, Stizostedion vitreum, Percidae | 75-400 | 145-830 | 1-3 | 72
red snapper, Lutjanus campechanus, Lutjanidae | 250 | 500 | 1 | -
sauger, Stizostedion canadense, Percidae | 500 | 500-1000 | 1 | -
Chinese catfish, Clarius fuscus, Clariidae | nt | 1816 | 1 | -
Footnotes:

Table 2: Tested Fish Species/Dose Combinations Found to be Safe
Nomenclature Common Name, Genus & Species, Family | Tested Dose(s) (IU/lb bw/injection) |  | Number of Injections | Injections Interval (h)
Nomenclature Common Name, Genus & Species, Family | Males | Females
white bass, Morone chrysops, Percichthyidae | 750 | 1500 | 1 | -
walleye, Stizostedion vitreum, Percidae | 750 | 1500 | 1 | -
grass carp, Ctenopharyngodon idella, Cyprinidae | 2500 | 5000 | 1 | -
channel catfish, Ictalurus punctatus, Ictaluridae | 2500 | 5000 | 1 | -

ADVERSE REACTIONS

Chorionic gonadotropin is a protein. In the unlikely event of an anaphylactic reaction, epinephrine should be administered. The administration of an antihistamine may also be indicated.

RESIDUE WARNINGS

No withdrawal period is required for cows or brood finfish treated according to label directions. The total dose administered (all injections combined) should not exceed 25,000 IU (25 mL) per fish in fish intended for human consumption.

STORAGE AND HANDLING PRECAUTIONS

Store at or below room temperature, 25°C (77°F). Keep out of reach of children. Once reconstituted, CHORULON® should be used immediately. Unused solution should be disposed of properly and not stored for future use.

HOW SUPPLIED

CHORULON® is supplied in cartons containing five vials of freeze-dried powder and five 10 mL vials of sterile diluent.

Distributed by Intervet Inc. (d/b/a Merck Animal Health), Rahway, NJ 07065.

Copyright © 2025 Merck & Co., Inc., Rahway, NJ, USA and its affiliates.

All rights reserved.

Made in Germany.

Rev. 10/2025

232977 R3 INU 240
05

PRINCIPAL DISPLAY PANEL - 5 vials Kit Carton

5 vials with diluent

chorulon®
(chorionic gonadotropin for injection)

MERCK
Animal Health